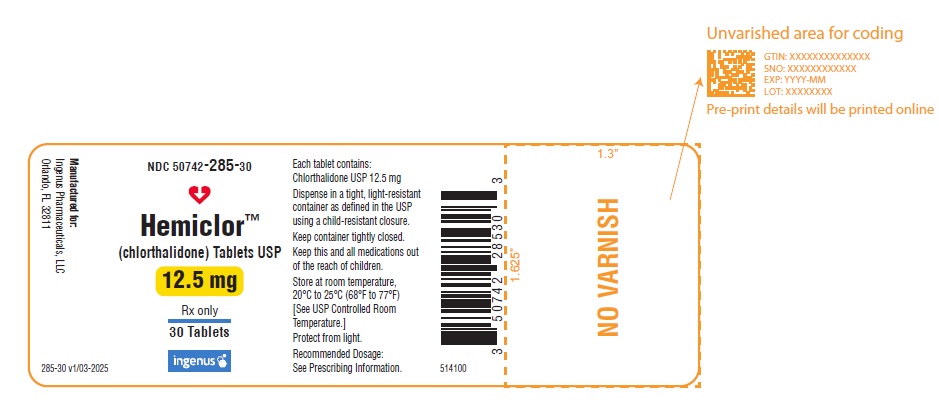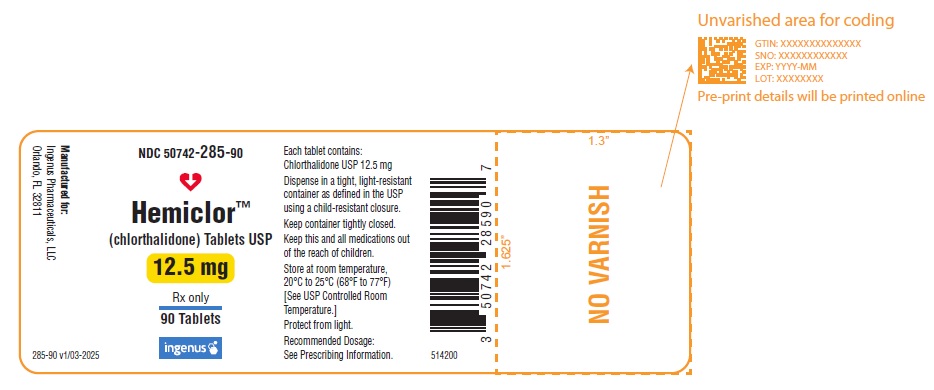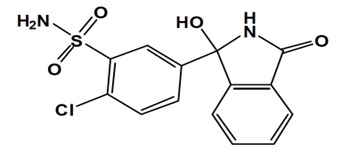 DRUG LABEL: HEMICLOR
NDC: 50742-285 | Form: TABLET
Manufacturer: Ingenus Pharmaceuticals, LLC
Category: prescription | Type: HUMAN PRESCRIPTION DRUG LABEL
Date: 20250327

ACTIVE INGREDIENTS: CHLORTHALIDONE 12.5 mg/1 1
INACTIVE INGREDIENTS: CALCIUM STEARATE; SILICON DIOXIDE; MICROCRYSTALLINE CELLULOSE; STARCH, CORN; SODIUM STARCH GLYCOLATE TYPE A

HIGHLIGHTS OF PRESCRIBING INFORMATION

These highlights do not include all the information needed to use HEMICLORTM safely and effectively. See full prescribing information for HEMICLOR.
HEMICLOR (chlorthalidone) tablets, for oral use
Initial U.S. Approval: 1960

1 INDICATIONS AND USAGE

HEMICLOR is a thiazide-like diuretic indicated for the treatment of hypertension in adults, to lower blood pressure. Lowering blood pressure reduces the risk of fatal and nonfatal cardiovascular events, primarily strokes and myocardial infarctions (1.1).

2 DOSAGE AND ADMINISTRATION

- The recommended starting dose is 12.5 mg or 25 mg orally once daily (2.1).
- Dose may be doubled after 2 to 4 weeks as needed based on individual response, up to a maximal dose of 100 mg once daily (2.1)

3 DOSAGE FORMS AND STRENGTHS

- Tablets: 12.5 mg (3).

4 CONTRAINDICATIONS

- Anuria (4).
- Hypersensitivity to chlorthalidone or other sulfonamide-derived drugs (4).

5 WARNINGS AND PRECAUTIONS

- Acute Kidney Injury: Patients with pre-existing kidney disease may be at higher risk. (5.1).
- Electrolyte Abnormalities: Monitor serum electrolytes periodically (5.2).
- Metabolic Disturbances (5.3).
- Systemic Lupus Erythematosus (5.4).

6 ADVERSE REACTIONS

The most frequently expected adverse drug reactions among patients receiving thiazide-like diuretics are electrolyte abnormalities and metabolic disturbances (6).

To report SUSPECTED ADVERSE REACTIONS, contact Ingenus Pharmaceuticals, LLC at 1-877-748-1970 or FDA at 1-800-FDA-1088 or www.fda.gov/medwatch.

7 DRUG INTERACTIONS

- Insulin requirements and oral hypoglycemic agent dosages may require adjustments (7).
- Possible increased responsiveness to tubocurarine (7).
- Possible decreased arterial responsiveness to norepinephrine (7).
- Lithium renal clearance is reduced by chlorthalidone, increasing the risk of lithium toxicity (7).

8 USE IN SPECIFIC POPULATIONS

- Pregnancy: May cause fetal harm (8.1).
- Lactation: Breastfeeding not recommended (8.2).
- Geriatric Use: No overall difference in responses versus younger patients, but care should be taken in dose selection in patients with impaired renal function (8.5).
- Hepatic Impairment: Alterations on fluid and electrolyte balance should be monitored in patients with hepatic impairment (8.6).

FULL PRESCRIBING INFORMATION

1 INDICATIONS AND USAGE

1.1 Hypertension

HEMICLOR is indicated for the treatment of hypertension in adults, to lower blood pressure.

Lowering blood pressure reduces the risk of fatal and nonfatal cardiovascular events, primarily strokes and myocardial infarctions. These benefits have been seen in controlled trials of antihypertensive drugs from a wide variety of pharmacologic classes including the class to which this drug principally belongs.

Control of high blood pressure should be part of comprehensive cardiovascular risk management, including, as appropriate, lipid control, diabetes management, antithrombotic therapy, smoking cessation, exercise, and limited sodium intake. Many patients will require more than one drug to achieve blood pressure goals. For specific advice on goals and management, see published guidelines, such as those of the National High Blood Pressure Education Program’s Joint National Committee on Prevention, Detection, Evaluation, and Treatment of High Blood Pressure (JNC).

Numerous antihypertensive drugs, from a variety of pharmacologic classes and with different mechanisms of action, have been shown in randomized controlled trials to reduce cardiovascular morbidity and mortality, and it can be concluded that it is blood pressure reduction, and not some other pharmacologic property of the drugs, that is largely responsible for those benefits. The largest and most consistent cardiovascular outcome benefit has been a reduction in the risk of stroke, but reductions in myocardial infarction and cardiovascular mortality also have been seen regularly.

Elevated systolic or diastolic blood pressure causes increased cardiovascular risk, and the absolute risk increase per mmHg is greater at higher blood pressures, so that even modest reductions of severe hypertension can provide substantial benefit. Relative risk reduction from blood pressure reduction is similar across populations with varying absolute risk, so the absolute benefit is greater in patients who are at higher risk independent of their hypertension (for example, patients with diabetes or hyperlipidemia), and such patients would be expected to benefit from more aggressive treatment to a lower blood pressure goal.

HEMICLOR may be used alone or in combination with other antihypertensives.

2 DOSAGE AND ADMINISTRATION

2.1 Recommended Dosage

Therapy should be initiated with the lowest possible dose. The recommended adult initial dose of HEMICLOR is 12.5 mg or 25 mg given orally with food once daily. Double the dosage every 2 to 4 weeks as needed based on individual patient response, up to a maximum of 100 mg once daily. Dosage above 100 mg daily usually does not increase effectiveness.

3 DOSAGE FORMS AND STRENGTHS

Each HEMICLOR tablet contains 12.5 mg of chlorthalidone. The tablets are white to off-white, modified rectangle shaped tablets debossed with “I” on one side and plain on the other side.

4 CONTRAINDICATIONS

Chlorthalidone is contraindicated in patients with anuria, or hypersensitivity to chlorthalidone or other sulfonamide-derived drugs.

5 WARNINGS AND PRECAUTIONS

5.1 Acute Kidney Injury

Monitor kidney function periodically. Diuretics can cause hypovolemia which may precipitate acute kidney injury. Patients with chronic kidney disease, heart failure, or volume depletion may be at particular risk of developing acute renal failure on Chlorthalidone. Consider withholding or discontinuing therapy in patients who develop a clinically significant decrease in kidney function while on chlorthalidone.

5.2 Electrolyte Abnormalities

Chlorthalidone can cause hypokalemia, hyponatremia, hypochloremic alkalosis, and hypomagnesemia. Hypomagnesemia can result in hypokalemia which appears difficult to treat despite potassium repletion. Hypokalemia is dose dependent. Monitor and correct serum electrolytes prior to use and monitor periodically.

5.3 Metabolic Disturbances

Chlorthalidone may increase blood sugar levels, affect diabetes control, and cause changes in the need for diabetes medication.

Chlorthalidone may raise serum levels of cholesterol and triglycerides. Monitor blood sugar and lipid levels.

Chlorthalidone may raise the serum uric acid level due to reduced clearance of uric acid and may cause or exacerbate hyperuricemia and precipitate gout in susceptible patients. Increases in serum uric acid are dose related.

Chlorthalidone decreases urinary calcium excretion and may cause elevations of serum calcium. Monitor calcium levels in patients with hypercalcemia receiving Chlorthalidone.

5.4 Systemic Lupus Erythematosus

The possibility of exacerbation or activation of systemic lupus erythematosus has been reported with thiazide diuretics, which are structurally related to chlorthalidone. However, systemic lupus erythematosus has not been reported following chlorthalidone administration.

6 ADVERSE REACTIONS

The following adverse reactions are described in more detail elsewhere in the label;

- Acute Kidney Injury [see Warnings and Precautions (5.1)]
- Electrolyte Abnormalities [see Warnings and Precautions (5.2)]
- Metabolic Disturbances [see Warnings and Precautions (5.3)]

The following adverse reactions have been observed with chlorthalidone, but there is not enough systematic collection of data to support an estimate of their frequency.

Gastrointestinal System Reactions: anorexia, gastric irritation, nausea, vomiting, cramping, diarrhea, constipation, jaundice (intrahepatic cholestatic jaundice), pancreatitis.

Central Nervous System Reactions: dizziness, paresthesias, headache.

Hematologic Reactions: leukopenia, agranulocytosis, thrombocytopenia, aplastic anemia.

Dermatologic-Hypersensitivity Reactions: purpura, photosensitivity, rash, urticaria, necrotizing angiitis (vasculitis) (cutaneous vasculitis), Lyell’s syndrome (toxic epidermal necrolysis).

Cardiovascular Reaction: Orthostatic hypotension.

Other Adverse Reactions: muscle spasm, weakness, restlessness, impotence, xanthopsia.

7 DRUG INTERACTIONS

Effect of chlorthalidone on other drugs

Insulin requirements in diabetic patients may be increased, decreased or unchanged. Higher dosage of oral hypoglycemic agents may be required.

Chlorthalidone may increase the responsiveness to tubocurarine.

Chlorthalidone may decrease arterial responsiveness to norepinephrine. This diminution is not sufficient to preclude effectiveness of the pressor agent for therapeutic use.

Lithium renal clearance is reduced by chlorthalidone, increasing the risk of lithium toxicity. Monitor serum lithium levels during concomitant use.

8 USE IN SPECIFIC POPULATIONS

8.1 Pregnancy

Risk Summary

Available data over decades from observational studies and reports with chlorthalidone use in pregnant women have not identified a drug-associated risk of major birth defects or miscarriage. However, adverse fetal outcomes, including fetal or neonatal jaundice, thrombocytopenia, hypoglycemia, and electrolyte abnormalities have been reported following maternal use of thiazide diuretics (see Clinical Considerations). Chlorthalidone should not be used as first-line therapy to treat hypertension in pregnancy. Advise pregnant women of the potential risk to a fetus.

The background risk of major birth defects and miscarriage for the indicated population is unknown. All pregnancies have a background risk of birth defect, loss, or other adverse outcomes. In the U.S. general population, the estimated background risks of major birth defects and miscarriage in clinically recognized pregnancies is 2 to 4% and 12.5 to 20%, respectively.

Clinical Considerations

Disease-associated maternal and/or embryo/fetal risk

Hypertension in pregnancy increases the maternal risk for pre-eclampsia, gestational diabetes, premature delivery, and delivery complications (e.g., need for cesarean section, and post-partum hemorrhage). Hypertension increases the fetal risk for intrauterine growth restriction and stillbirth.

Fetal/Neonatal Adverse Reactions

Thiazides can cross the placenta, and concentrations reached in the umbilical vein approach those in the maternal plasma. Thiazides, like other diuretics, can cause placental hypoperfusion. Use of thiazides during pregnancy is associated with a risk of fetal or neonatal jaundice, thrombocytopenia, hypoglycemia, and electrolyte abnormalities. Thiazides do not prevent or alter the course of EPH (Edema, Proteinuria, Hypertension) gestosis (pre-eclampsia) and should not be used as first-line therapy to treat hypertension in pregnant women.

Animal Data

Reproduction studies have been performed in the rat and the rabbit and have revealed no evidence of harm to the fetus due to chlorthalidone. The available data do not allow the calculation of comparisons between the exposure of chlorthalidone observed in animal studies to the systemic exposure that would be expected in humans.

8.2 Lactation

Risk Summary

Chlorthalidone is present in human milk. There is no information regarding the effects of chlorthalidone on the breastfed infant or the effects on milk production. Because of the potential for chlorthalidone accumulation which may lead to serious adverse reactions in the breastfed infant (such as jaundice, thrombocytopenia, hyperglycemia, electrolyte abnormalities), advise patients that breastfeeding is not recommended during treatment with chlorthalidone.

8.4 Pediatric Use

Safety and effectiveness in children have not been established.

8.5 Geriatric Use

In general, dose selection for an elderly patient should be cautious, usually starting at the low end of the dosing range, reflecting the greater frequency of decreased hepatic, renal or cardiac function, and of concomitant disease or other drug therapy.

Chlorthalidone is known to be substantially excreted by the kidney, and the risk of toxic reactions to this drug may be greater in patients with impaired renal function. Because elderly patients are more likely to have decreased renal function, care should be taken in dose selection, and it may be useful to monitor renal function.

8.6 Hepatic Impairment

Minor alterations of fluid and electrolyte balance may precipitate hepatic coma in patients with impaired hepatic function or progressive liver disease.

10 OVERDOSAGE

Symptoms of acute overdosage include nausea, weakness, dizziness and disturbances of electrolyte balance. The oral LD50 of the drug in the mouse and the rat is more than 25,000 mg/kg body weight. The minimum lethal dose (MLD) in humans has not been established. There is no specific antidote but gastric lavage is recommended, followed by supportive treatment. Where necessary, this may include intravenous dextrose-saline with potassium, administered with caution.

11 DESCRIPTION

HEMICLOR (chlorthalidone) is an antihypertensive/diuretic supplied as 12.5 mg tablets for oral use. Chlorthalidone is a monosulfamyl diuretic that differs chemically from thiazide diuretics in that a double ring system is incorporated in its structure. It is a racemic mixture of 2-chloro-5-(1-hydroxy-3-oxo-1-isoindolinyl) benzenesulfonamide, with the following structural formula:

Molecular Formula: C14H11ClN2O4S Molecular Weight: 338.8 g/mol

Chlorthalidone is practically insoluble in water, soluble in acetone and in methanol, slightly soluble in 96% ethanol, practically insoluble in dichloromethane. It dissolves in diluted solutions of alkali hydroxides.

Each HEMICLOR tablet contains the following inactive ingredients: calcium stearate, colloidal silicon dioxide, microcrystalline cellulose, pregelatinized starch and sodium starch glycolate.

12 CLINICAL PHARMACOLOGY

12.1 Mechanism of Action

Chlorthalidone is a long-acting oral diuretic with antihypertensive activity. Chlorthalidone produces diuresis with increased excretion of sodium and chloride. The site of action appears to be the cortical diluting segment of the ascending limb of Henle’s loop of the nephron. The diuretic effects of chlorthalidone lead to decreased extracellular fluid volume, plasma volume, cardiac output, total exchangeable sodium, glomerular filtration rate, and renal plasma flow. Although the mechanism of action of chlorthalidone and related drugs is not wholly clear, sodium and water depletion appear to provide a basis for its antihypertensive effect.

12.2 Pharmacodynamics

The diuretic action of chlorthalidone commences a mean of 2.6 hours after dosing and continues for up to 72 hours. Chlorthalidone produces dose-related reductions in serum potassium levels, elevations in serum uric acid and blood glucose, and it can lead to decreased sodium and chloride levels.

12.3 Pharmacokinetics

Distribution

Approximately 75 percent of the drug is bound to plasma proteins, 58 percent of the drug being bound to albumin. This is caused by an increased affinity of the drug to erythrocyte carbonic anhydrase. Data are not available regarding concentration of the drug in body fluids, degree of uptake by a particular organ or in the fetus, or passage across the blood-brain barrier.

Elimination

The mean plasma half-life of chlorthalidone is about 40 to 60 hours.

Metabolism

Data are not available regarding percentage of dose as unchanged drug and metabolites.

Excretion

Chlorthalidone is eliminated primarily as unchanged drug in the urine. Nonrenal routes of elimination have yet to be clarified.

13 NONCLINICAL TOXICOLOGY

13.1 Carcinogenesis, Mutagenesis, Impairment of Fertility

No carcinogenicity study has been conducted with chlorthalidone.

Mutagenesis: Chlorthalidone demonstrated no potential for mutagenic effects at non-cytotoxic concentrations and is considered not to pose a mutagenic risk to humans.

Impairment of Fertility: Chlorthalidone at a dosage of 100 mg/kg had no effect on fertility in rats.

14 CLINICAL STUDIES

The efficacy of a once daily dose of chlorthalidone 12.5 mg for the treatment of hypertension in adults is derived from a published randomized, double-blind, multinational, study (Sica et al, 2012) [Sica D, Bakris GL, White WB, et al. J.Clin. Hypertens. 2012;14(5):284-292] along with other supportive studies from the published literature.

16 HOW SUPPLIED/STORAGE AND HANDLING

HEMICLOR 12.5 mg tablets are supplied as white to off-white, modified rectangle shaped tablets debossed with “I” on one side and plain on the other side. HEMICLOR tablets are supplied as bottles of 30 tablets, 90 tablets, 100 tablets and 1,000 tablets.

NDC Number: 50742-285-30, Bottles of 30.

NDC Number: 50742-285-90, Bottles of 90.

NDC Number: 50742-285-01, Bottles of 100.

NDC Number: 50742-285-10, Bottles of 1,000.

Storage

Store at 20ºC to 25ºC (68ºF to 77ºF) [See USP Controlled Room Temperature].

Dispense in a tight, light-resistant container as defined in the USP using a child-resistant closure.

17 PATIENT COUNSELING INFORMATION

Patients should inform their doctor if they have had an allergic reaction to chlorthalidone or other diuretics; kidney disease; gout; been taking lithium carbonate.

Patients should be cautioned to contact their physician if they experience any of the following symptoms of potassium loss: excess thirst, tiredness, drowsiness, restlessness, muscle pains or cramps, nausea, vomiting or increased heart rate or pulse.

Pregnancy

Advise a pregnant woman of the potential risk to a fetus. Advise females of reproductive potential to inform their prescriber of a known or suspected pregnancy [see Use in Specific Populations (8.1)].

Lactation

Advise females not to breastfeed during treatment with chlorthalidone [see Use in Specific Populations (8.2)].

Rx Only

Manufactured for:

Ingenus Pharmaceuticals, LLC
Orlando, FL 32811

Rev. 03/2025
555800

Principal Display Panel - 30 Tablets

NDC 50742-285-30

HemiclorTM

(chlorthalidone) Tablets USP

12.5 mg

Rx only

30 Tablets

ingenus

Principal Display Panel - 90 Tablets

NDC 50742-285-90

HemiclorTM

(chlorthalidone) Tablets USP

12.5 mg

Rx only

90 Tablets

ingenus